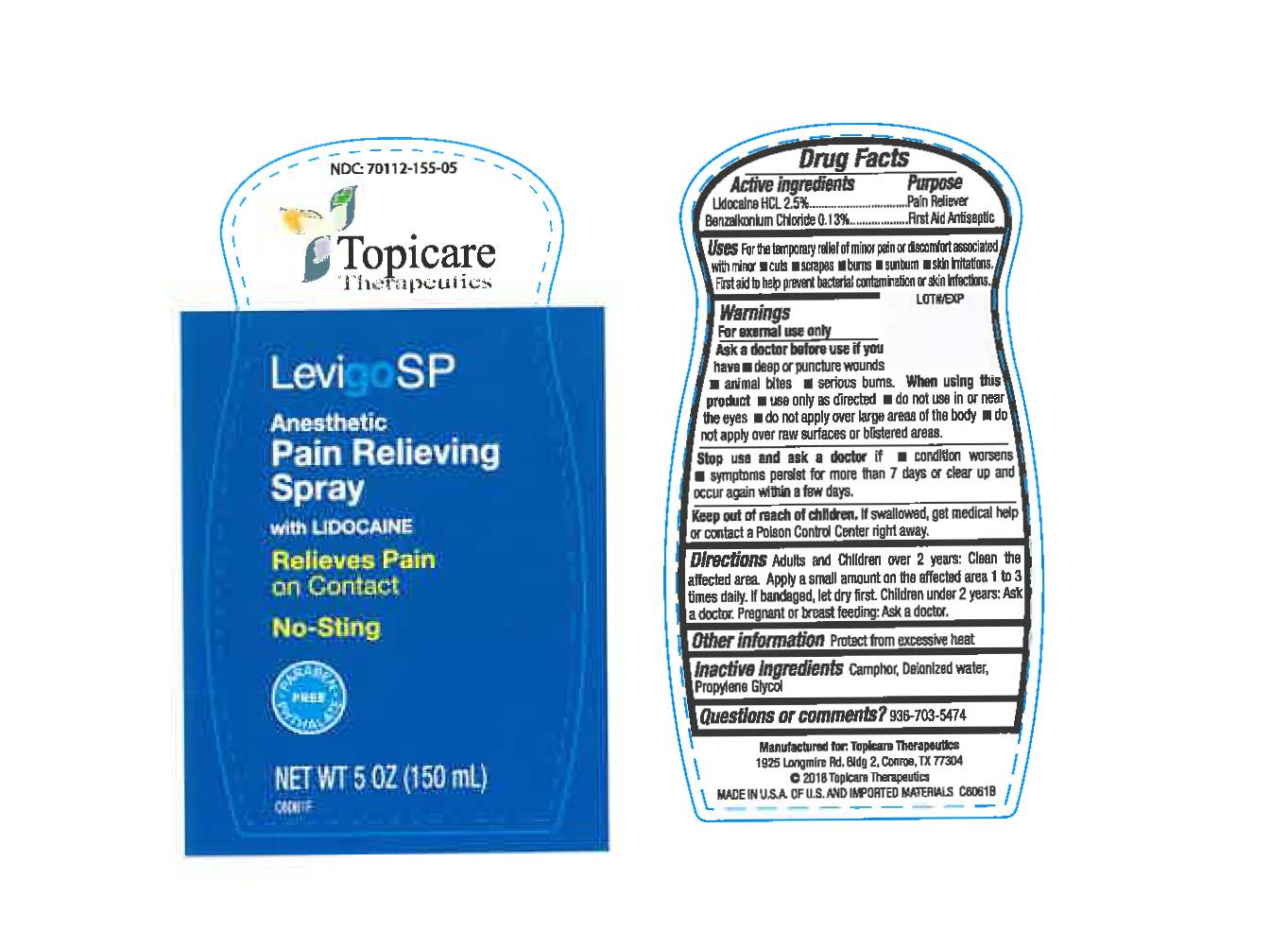 DRUG LABEL: LevigoSP
NDC: 70112-155 | Form: SPRAY
Manufacturer: Topicare Management, LLC
Category: otc | Type: HUMAN OTC DRUG LABEL
Date: 20180809

ACTIVE INGREDIENTS: BENZALKONIUM CHLORIDE 0.13 mg/1 mL; LIDOCAINE HYDROCHLORIDE 2.5 mg/1 mL
INACTIVE INGREDIENTS: WATER; CAMPHOR (NATURAL); PROPYLENE GLYCOL

Description

LevigoSP is a Lidocaine HCL 2.5% and Benzalkonium Chloride 0.13% topical anesthetic spray indicated to temporarily relieve minor pain.

Active Ingredients

Lidocaine HCL 2.5% --- Pain Reliever

Benzalkonium Chloride 0.13% --- First Aid Antiseptic

Purpose

For the temporary relief of minor pain or discomfort associated with minor: cuts, scrapes, burns, sunburn, skin irritations. First aid to prevent bacterial contamination or skin infections.

Warnings

For external use only.

Ask Doctor

Ask a doctor before use if you have: *deep or puncture wounds *animal bites *serious burns.

When using this product: *use only as directed *do not use in or near the eyes *do not apply over large areas of the body *do not apply over raw surfaces or blistered areas.

Stop Use

Stop use and ask a doctor if: *condition worsens *symptoms persist for more than 7 days or clear up and occur again within a few days.

Keep out of reach of children. If swallowed, get medical help or contact a Poison Control Center right away.

Indications & Usage

Directions:

Adults and Children over 2 years: Clean the affected area, apply a small amount on the affected area 1 to 3 times daily. If bandaged, let dry first.

Children under 2 years: Ask a doctor.

Pregnant or breast feeding: Ask a doctor.

Dose & Administration

Manufactured By:

Wisconsin Pharmacal Co.

1 Pharmacal Way

Jackson, WI 53037

Made in the U.S.A. of U.S. and imported materials.

Manufactured For:

Topicare Therapeutics

1925 Longmire Rd.

Bldg. 2

Conroe, TX 77304

Net Wt. 5 FL OZ (150Ml) bottle

Questions or Comments

For questions or comments, call 1-936-703-5474.

Inactive Ingredients

Camphor, Deionized water, Propylene Glycol

Storage & Handling

Protect from excessive heat.